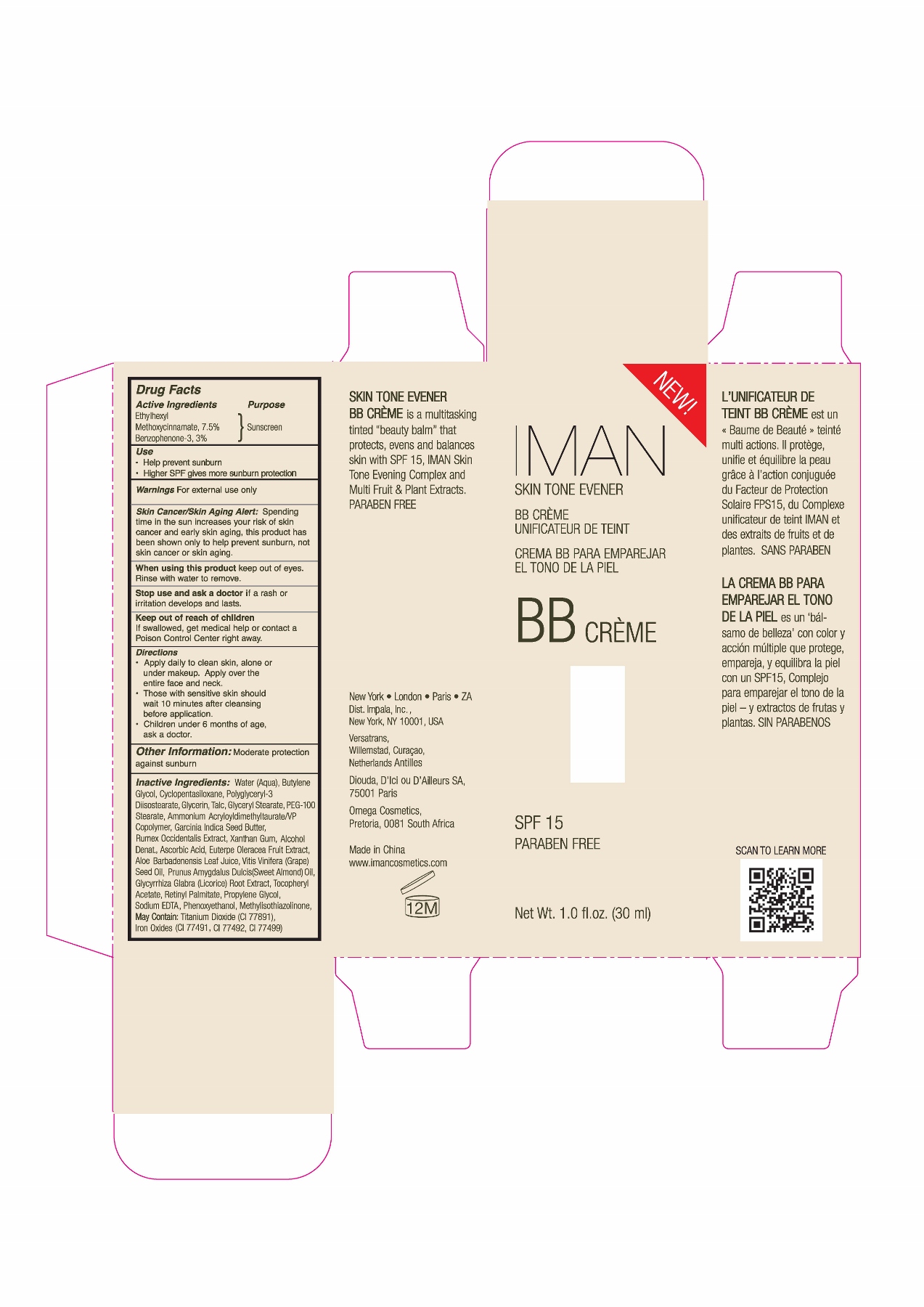 DRUG LABEL: Iman Skin Tone Evener BB SPF 15
NDC: 43438-003 | Form: CREAM
Manufacturer: Impala, Inc.
Category: otc | Type: HUMAN OTC DRUG LABEL
Date: 20120815

ACTIVE INGREDIENTS: OXYBENZONE 3 g/100 mL; OCTINOXATE 7.5 g/100 mL
INACTIVE INGREDIENTS: VITAMIN A PALMITATE; ALMOND OIL; XANTHAN GUM; ASCORBIC ACID; PROPYLENE GLYCOL; WATER 38.83 g/100 mL; PHENOXYETHANOL; METHYLISOTHIAZOLINONE; GLYCERYL MONOSTEARATE; TITANIUM DIOXIDE; FERRIC OXIDE RED; 1,2-BUTANEDIOL; ALPHA-TOCOPHEROL; EDETATE DISODIUM; FERRIC OXIDE YELLOW; ALOE VERA LEAF; CYCLOMETHICONE 5; PEG-100 STEARATE; GLYCYRRHIZA GLABRA; GLYCERIN; POLYGLYCERYL-3 DIISOSTEARATE; ACAI; GRAPE SEED OIL; TALC; ALCOHOL; AMMONIUM ACRYLOYLDIMETHYLTAURATE/VP COPOLYMER; GARCINIA INDICA SEED BUTTER

Drug Fact

Active Ingredient:

Benzophenone-3: 3%

Octyl methoxycinnamate: 7.5%

Purpose:

Sunscreen

Uses:

Help prevent sunburn

Warning:

For external use only

Skin Cancer/Skin Aging Alert:

Spending time in the sun increases your risk of skin cancer and early skin aging. This product has been shown to only help prevent sunburn, not skin cancer and skin aging.

Do not use on damaged or broken skin.

When Using This Product:

Keep out of eyes. Rinse with water to remove.

Stop use and ask a doctor if rash or irritation develops and lasts

Keep Out Of Reach Of Children. If swallowed, get medical help or contact a Poison Control Center immediately.

Directions:

Apply daily to clean skin, alone or under makeup. Apply over the entire face and neck.

These with sensitive skin should wait 10 minutes after cleansing before application.

Children under 6 months of age, ask a doctor.

Other Information
Moderate protection against sunburn

Inactive Ingredient:

Water (Aqua), Butylene Glycol, Cyclopentasiloxane, Polyglyceryl-3 Diisostearate, Glycerin, Talc, Glyceryl Stearate, PEG-100 Stearate, Ammonium Acryloyldimethyltaurate/VP Copolymer, Garcinia Indica Seed Butter, Rumex Occidentalis Extract,Xanthan Gum, Alcohol Denat, Ascorbic Acid, Euterpe Oleracea Fruit Extract, Aloe Barbadenensis Leaf Juice, Vitis Vinifera (Grape) Seed Oil, Prunus Amygdalus Dulcis (Sweed Almond) Oil, Glycyrrhiza Blabra (Licorice) Root Extract, Tocopheryl Acetate, Retinyl Palmitate, Propyl Glycol, Sodium EDTA, Phenoxyethanol, Methylisothiazolinone.

May Contain: Titanium Dioxide (CI 77891), Iron Oxides (CI 77491, CI 77492, CI 77499)

PACKAGE LABEL

lab